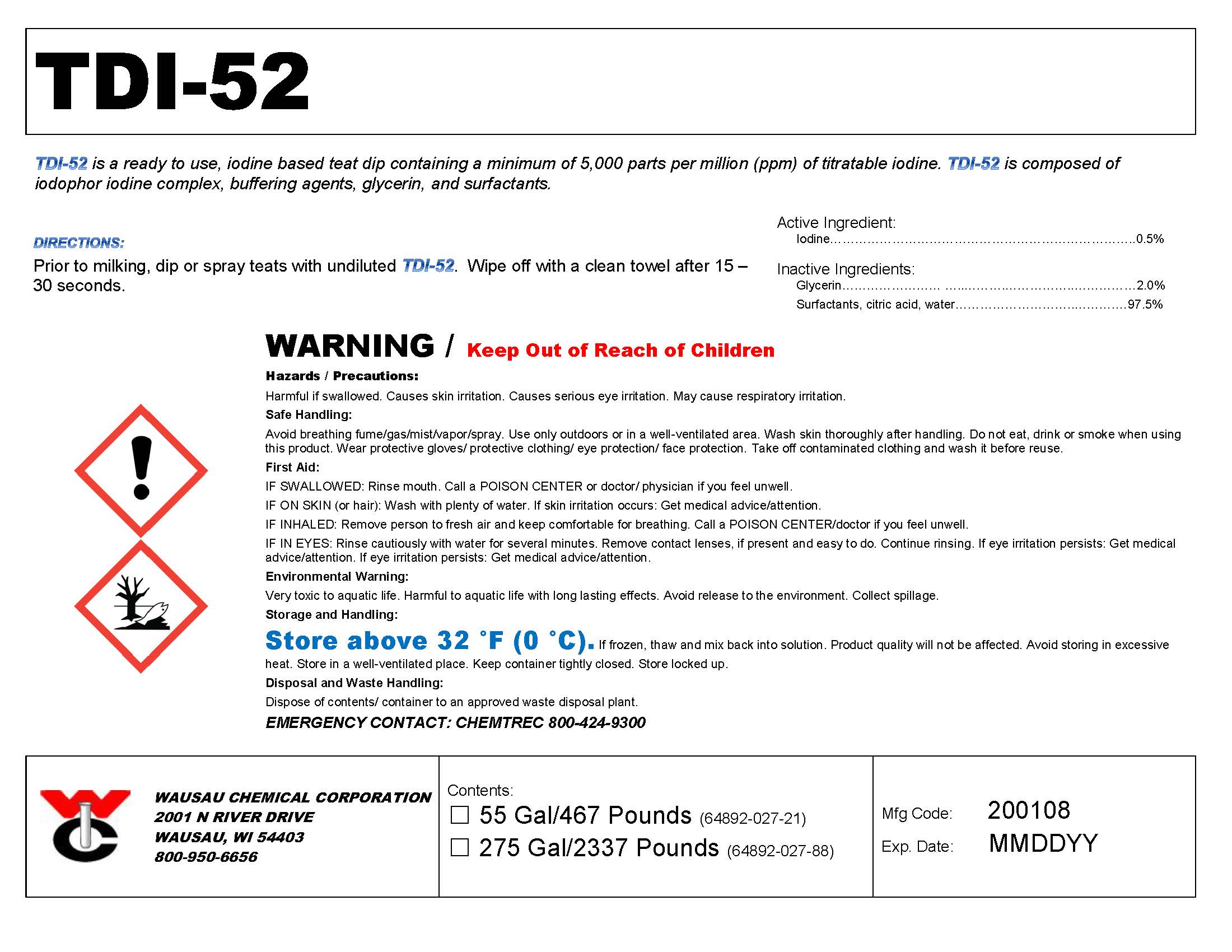 DRUG LABEL: TDI-52
NDC: 64892-027 | Form: SOLUTION
Manufacturer: Wausau Chemical
Category: animal | Type: OTC ANIMAL DRUG LABEL
Date: 20200205

ACTIVE INGREDIENTS: Iodine 5000 mg/1 L

TDI-52 Iodine Teat Dip

DISPOSAL AND WASTE HANDLING

Dispose of contents/container to an approved waste disposal plant.

ENVIRONMENTAL WARNING

Very toxic to aquatic life. Harmful to aquatic life with long lasting effects. Avoid release to the environment. Collect spillage.

GENERAL PRECAUTIONS

WARNING / Keep Out of Reach of Children

First Aid:

IF SWALLOWED: Rinse mouth. Call a POISON CENTER or doctor/ physician if you feel unwell.

IF ON SKIN (or hair): Wash with plenty of water. If skin irritation occurs: Get medical advice/attention.

IF INHALED: Remove person to fresh air and keep comfortable for breathing. Call a POISON CENTER/doctor if you feel unwell.

IF IN EYES: Rinse cautiously with water for several minutes. Remove contact lenses, if present and easy to do. Continue rinsing. If eye irritation persists: Get medical advice/attention. If eye irritation persists: Get medical advice/attention.

SAFE HANDLING WARNING

Avoid breathing fume/gas/mist/vapor/spray. Use only outdoors or in a well-ventilated area. Wash skin thoroughly after handling. Do not eat, drink or smoke when using this product. Wear protective gloves/ protective clothing/ eye protection/ face protection. Take off contaminated clothing and wash it before reuse.

STORAGE AND HANDLING

Store above 32 °F (0 °C). If frozen, thaw and mix back into solution. Product quality will not be affected.

Avoid storing in excessive heat. Store in a well-ventilated place. Keep container tightly closed. Store locked up

DIRECTIONS:

Prior to milking, dip or spray teats with undiluted TDI-52. Wipe off with a clean towel after 15 – 30 seconds.

Active Ingredient:
Iodine………………………………………………………………0.5%

Wausau Chemical Corporation

2001 N River Drive

Wausau, WI 54403

800-950-6656